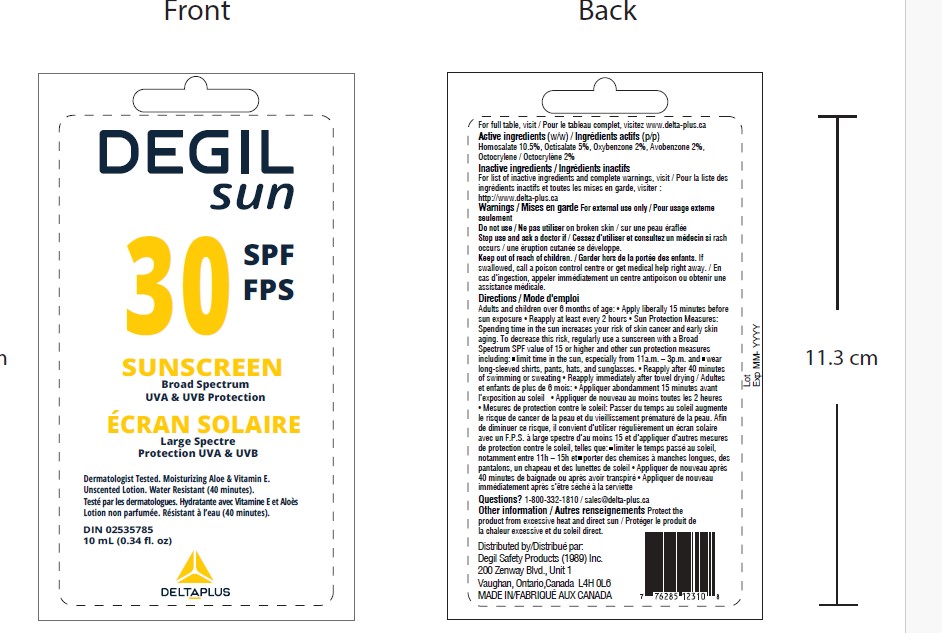 DRUG LABEL: Degil Sun SPF 30 Sunscreen
NDC: 58331-060 | Form: LOTION
Manufacturer: Degil Safety Products (1989) Inc
Category: otc | Type: HUMAN OTC DRUG LABEL
Date: 20240424

ACTIVE INGREDIENTS: OXYBENZONE 2 g/100 mL; OCTISALATE 5 g/100 mL; AVOBENZONE 2 g/100 mL; HOMOSALATE 10.5 g/100 mL; OCTOCRYLENE 2 g/100 mL
INACTIVE INGREDIENTS: PALMITIC ACID; DIMETHICONE; SORBITOL; METHYLPARABEN; EDETATE DISODIUM; ALOE VERA LEAF; BARIUM SULFATE; ACRYLATES/OCTYLACRYLAMIDE COPOLYMER (40000 MW); TROLAMINE; PROPYLPARABEN; SORBITAN ISOSTEARATE; ALPHA-TOCOPHEROL; POLYGLYCERYL-3 DISTEARATE; BENZYL ALCOHOL; JOJOBA OIL; CARBOMER HOMOPOLYMER, UNSPECIFIED TYPE; PROPYLENE GLYCOL; WATER; STEARIC ACID; VINYLPYRROLIDONE/EICOSENE COPOLYMER

Degil Sun SPF30 Sunscreen

DOSAGE AND ADMINISTRATION

Lotion

Topical

ACTIVE INGREDIENT

Homosalate 10.5%, Octisalate 5%, Oxybenzone 2%, Avobenzone 2%,
Octocrylene 2%

PURPOSE

Sunscreen

INDICATIONS AND USAGE

Sun Protection Factor 30 • SPF 30 • Helps prevent sunburn • Sunburn protectant

Helps protect from sunburn • If used as directed with other sun protection measures [see Directions (for Use)], decreases the risk of skin cancer and early skin aging caused by the sun • Water Resistant (40 minutes.

WARNINGS

For external use only

Do not use on broken skin

When using this product avoid contact with eyes. If contact occurs, rinse thoroughly with water

Stop use and ask a doctor if rash occurs

Keep out of reach of children. If swallowed, call a poison control centre or get medical help right away

Keep out of reach of children

INSTRUCTIONS FOR USE

Adults and children over 6 months of age • Apply liberally/generously (and evenly) 15 minutes before sun exposure • Reapply at least every 2 hours • Sun Protection Measures: Spending time in the sun increases your risk of skin cancer and early skin aging. To decrease this risk, regularly use a sunscreen with a Broad Spectrum SPF value of 15 or higher and other sun protection measures including: ▪ limit time in the sun, especially from 11 a.m. – 3 p.m.; and ▪ wear long-sleeved shirts, pants, hats and sunglasses • Reapply after 40 minutes of swimming or sweating • Reapply immediately after towel drying

INACTIVE INGREDIENT

Aqua,Sorbitol, Sorbitan Isostearate, Polyglyceryl-3 Distearate, Barium Sulfate, Acrylates / Octylacrylamide Copolymer, Palmitic acid, Triethanolamine, Stearic acid, Benzyl Alcohol, VP/Eicosene Copolymer, Dimethicone, Carbomer, Methyl paraben, Aloe Barbadensis Leaf Extract, Simmondsia Chinensis (Jojoba) Seed Oil, Vitamin E, Propylparaben, Disodium EDTA, Propylene glycol

Other information

Protect the product from excessive heat and direct sun

Questions? 1-800-332-1810 / sales@delta-plus.ca

PACKAGE LABEL

DEGIL Sun SPF 30 Sunscreen

Broad Spectrum

UVA&UVB Protection

Dermatologist Tested. Moisutrizing Aloe & Vitamin E.

Unscented Lotion. Water Resistant (40 minutes)

DIN 02535785